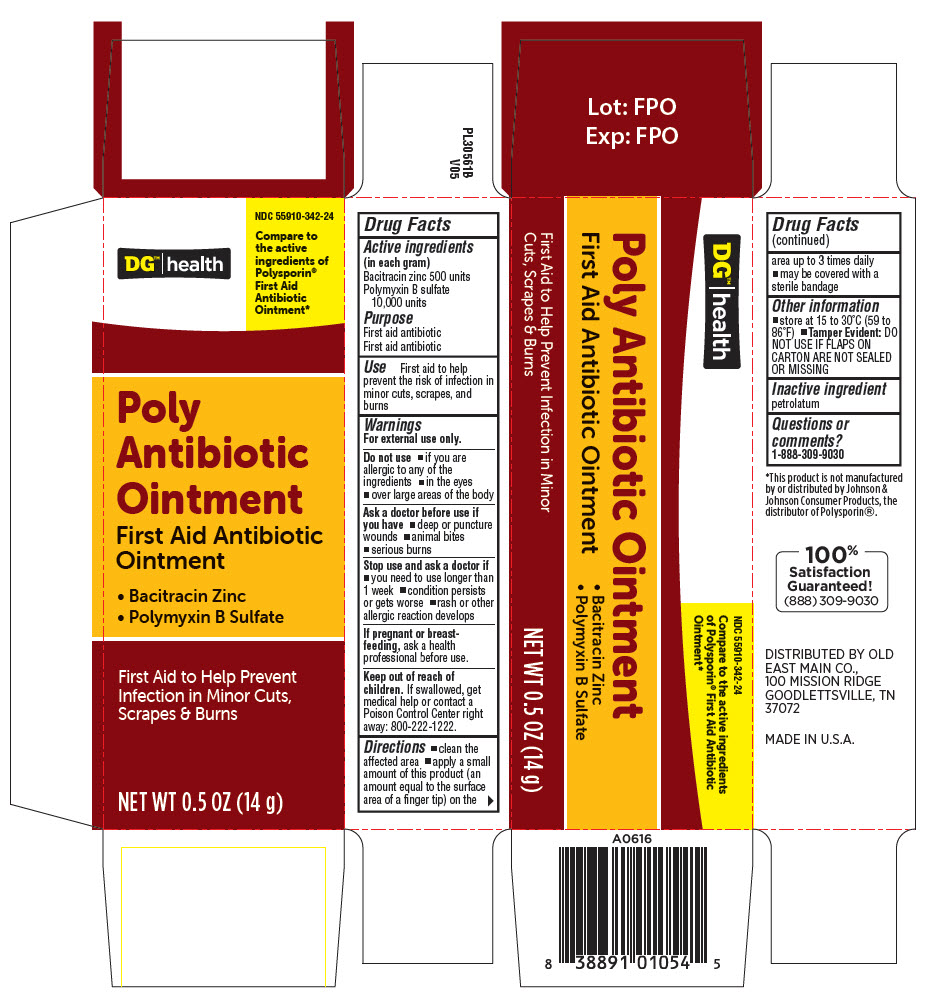 DRUG LABEL: DG Poly Antibiotic 
NDC: 55910-342 | Form: OINTMENT
Manufacturer: Dollar General
Category: otc | Type: HUMAN OTC DRUG LABEL
Date: 20250702

ACTIVE INGREDIENTS: Bacitracin 500 U/1 g; POLYMYXIN B SULFATE 10000 U/1 g
INACTIVE INGREDIENTS: petrolatum

DG Poly Antibiotic Ointment
First Aid Antibiotic Ointment

Drug Facts

ACTIVE INGREDIENT

Active ingredients (in each gram) | Purpose
Bacitracin zinc 500 units | First aid antibiotic
Polymyxin B sulfate 10,000 units | First aid antibiotic

Use

First aid to help prevent the risk of infection in minor cuts, scrapes, and burns

Warnings

For external use only.

Do not use

- if you are allergic to any of the ingredients
- in the eyes
- over large areas of the body

Ask a doctor before use if you have

- deep or puncture wounds
- animal bites
- serious burns

Stop use and ask a doctor if

- you need to use longer than 1 week
- condition persists or gets worse
- rash or other allergic reaction develops

PREGNANCY OR BREAST FEEDING

If pregnant or breast-feeding, ask a health professional before use.

Keep out of reach of children. If swallowed, get medical help or contact a Poison Control Center right away: 800-222-1222.

Directions

- clean the affected area
- apply a small amount of this product (an amount equal to the surface area of a finger tip) on the area up to 3 times daily
- may be covered with a sterile bandage

Other information

- store at 15 to 30°C (59 to 86°F)
- Tamper Evident: DO NOT USE IF FLAPS ON CARTON ARE NOT SEALED OR MISSING

Inactive ingredient

petrolatum

Questions or comments?

1-888-309-9030

DISTRIBUTED BY OLD
EAST MAIN CO.,
100 MISSION RIDGE
GOODLETTSVILLE, TN
37072

PRINCIPAL DISPLAY PANEL - 14 g Tube Carton

DG™|health

NDC 55910-342-24

Compare to
the active
ingredients of
Polysporin®
First Aid
Antibiotic
Ointment*

Poly
Antibiotic
Ointment
First Aid Antibiotic
Ointment

- Bacitracin Zinc
- Polymyxin B Sulfate

First Aid to Help Prevent
Infection in Minor Cuts,
Scrapes & Burns

NET WT 0.5 OZ (14 g)